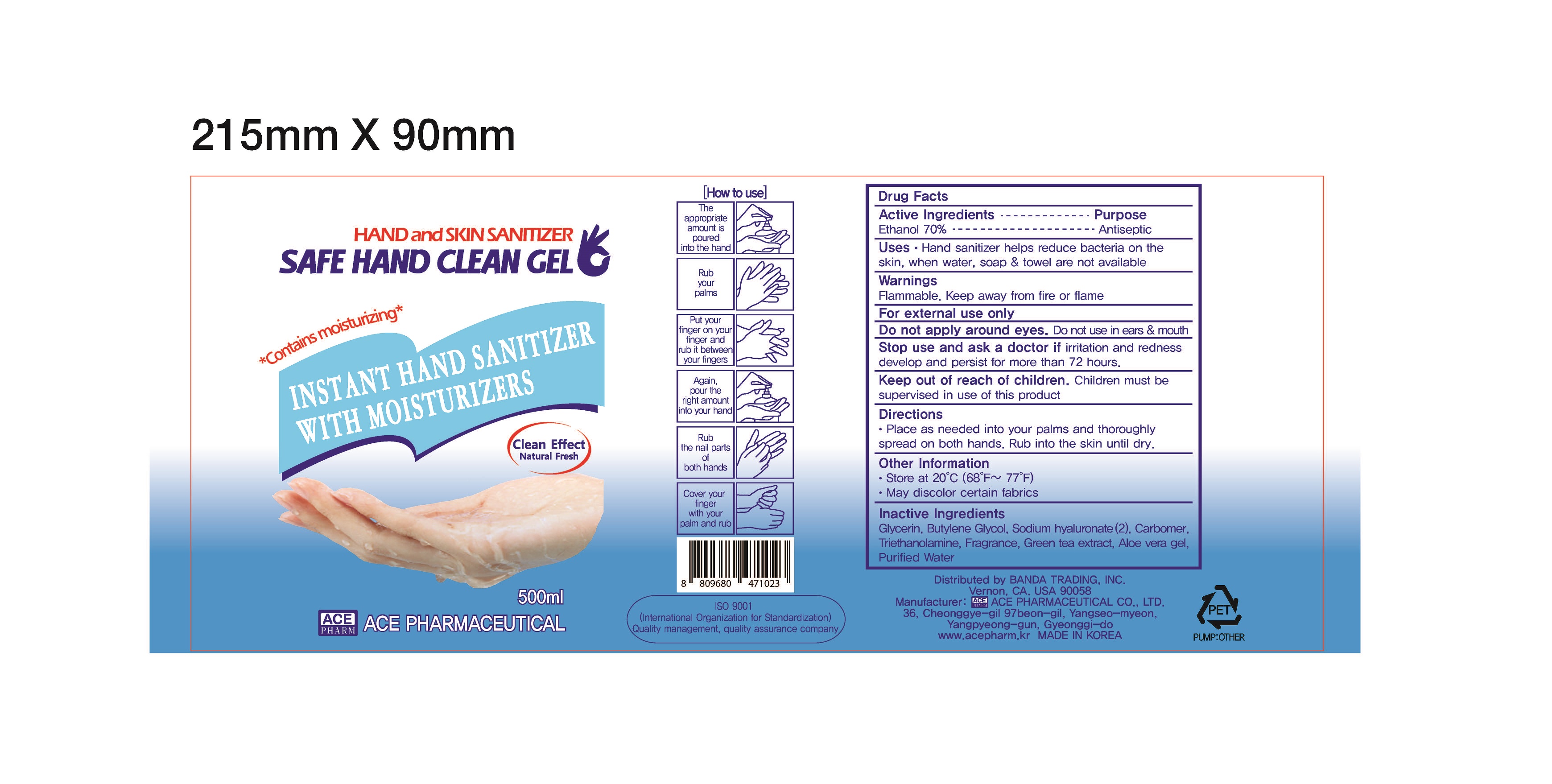 DRUG LABEL: SAFE HAND CLEAN gel
NDC: 74196-0003 | Form: GEL
Manufacturer: ACE PHARMACEUTICAL CO LTD
Category: otc | Type: HUMAN OTC DRUG LABEL
Date: 20200507

ACTIVE INGREDIENTS: ALCOHOL 70 g/100 mL
INACTIVE INGREDIENTS: GLYCERIN; TROLAMINE; WATER; BUTYLENE GLYCOL

Drug Facts

ACTIVE INGREDIENT

ethanol

INACTIVE INGREDIENT

Glycerin
Butylene Glycol
Sodium Hyaluronate
Carbomer
Triethanolamine
Fragrance
Camellia Sinensis Leaf Extract
Aloe Barbadensis Leaf Juice
Water

PURPOSE

hand sanitizer to help reduce bacteria that potentially can cause disease

for use when soap and water are not available

KEEP OUT OF REACH OF THE CHILDREN

INDICATIONS AND USAGE

Apply to clean, dry hands. Apply sufficient amount to thoroughly wet all surfaces of hands and fingers. Rub onto hands until dry.

Supervise children in the use of this product.

Dispense appropriate amount on your palm and thoroughly spread on both hands and rub into the skin until dry

WARNINGS

For external use only.

Flammable, keep away from fire or flame.

When using this product keep out of eyes. If contact with eyes occurs, rinse promptly and thoroughly with water.

Stop use and ask a doctor if significant irritation or sensitization develops.

Keep out of reach of children. If swallowed, get medical help or contact a Poison Control Center right away.

DOSAGE AND ADMINISTRATION

for external use only